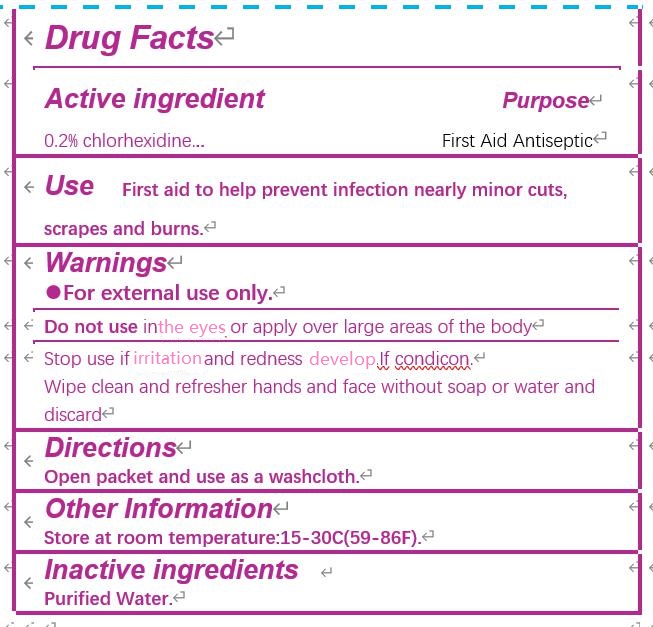 DRUG LABEL: PRE-MOISTENED TOWELETTE
NDC: 80514-004 | Form: SWAB
Manufacturer: JIANGSU HAIDA INTERNATIONAL TRADING CO., LTD.
Category: otc | Type: HUMAN OTC DRUG LABEL
Date: 20200903

ACTIVE INGREDIENTS: CHLORHEXIDINE GLUCONATE 0.2 g/100 g
INACTIVE INGREDIENTS: WATER

Active ingredient

Chlorhexidine Gluconate 0.2%

Purpose

First Aid Antiseptic

CAUTION: Keep out of reach of children

If swallowed, get medical help or contact Poison Control Center right away.

Use

First aid to help prevent infection nearly minor cuts,scrapes and burns.

Warnings

For external use only.

Do not use

in the eyes or apply over large areas of the body.

Stop use

If irritation and redness develop.

Ask a doctor

If condition persists or gets worse.

Directions

Open packet and use as a washcloth.

Inactive ingredients

Purified water